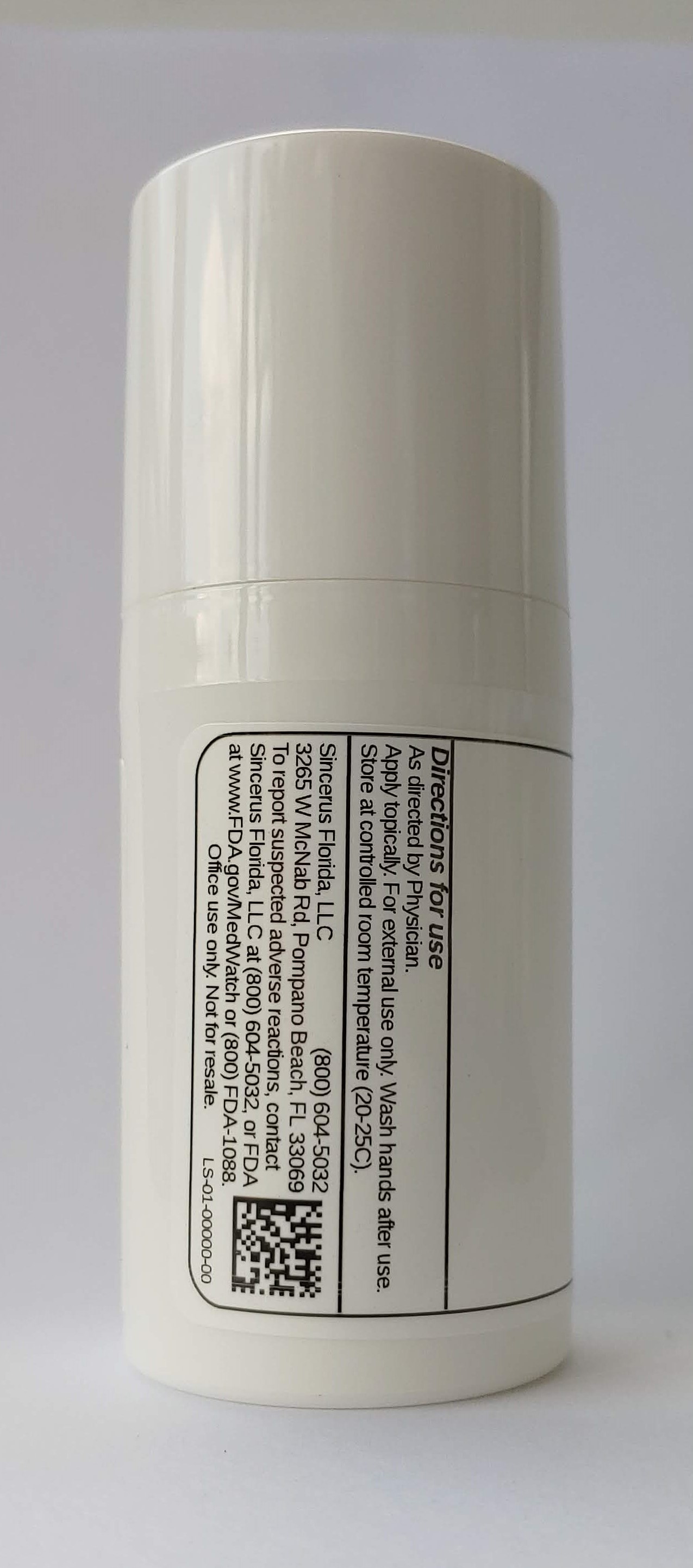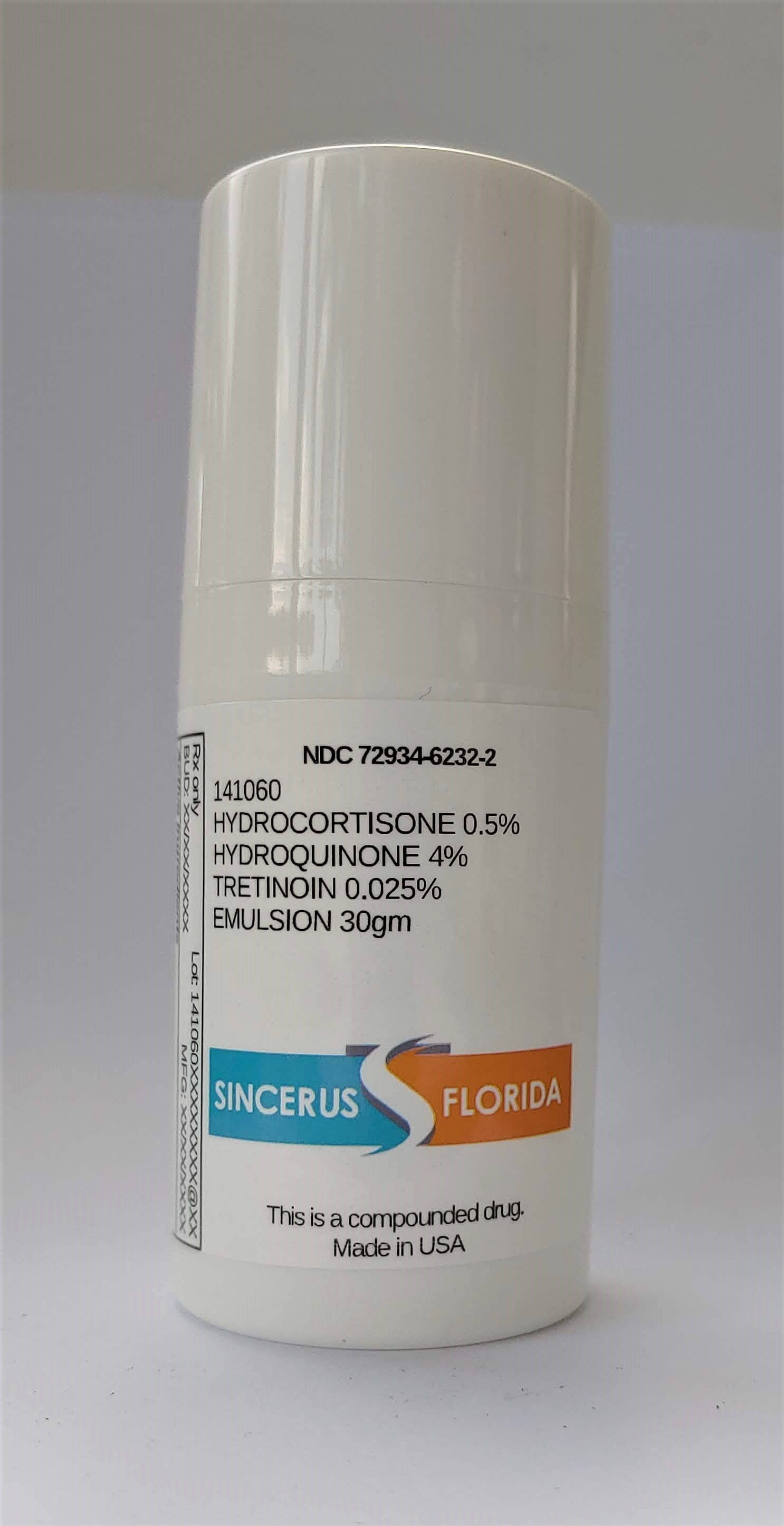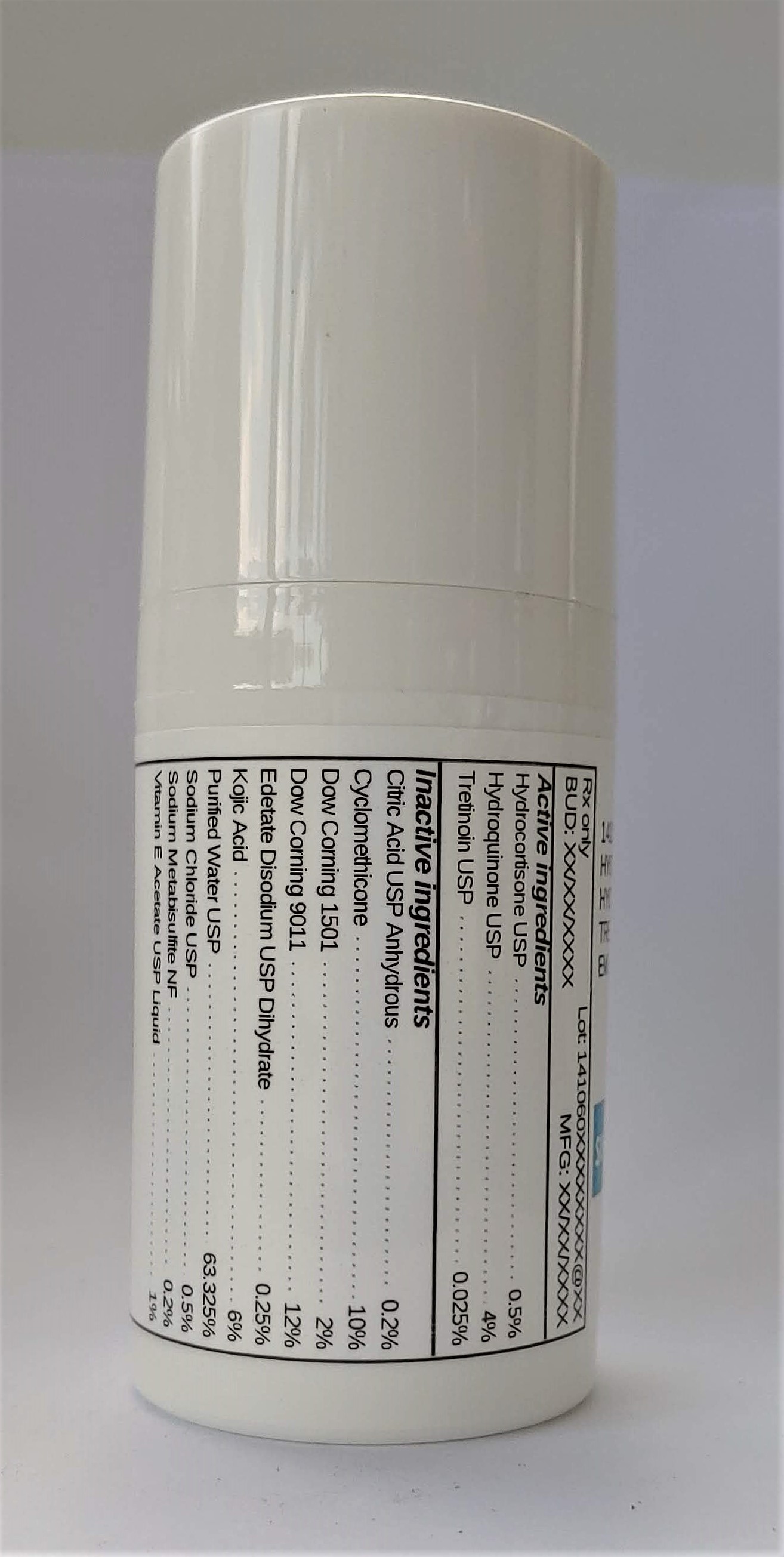 DRUG LABEL: 141060 HYDROCORTISONE 0.5% / HYDROQUINONE 4% / TRETINOIN 0.025%
NDC: 72934-6232 | Form: EMULSION
Manufacturer: Sincerus Florida, LLC
Category: prescription | Type: HUMAN PRESCRIPTION DRUG LABEL
Date: 20200702

ACTIVE INGREDIENTS: TRETINOIN 0.025 g/100 g; HYDROCORTISONE 0.5 g/100 g; HYDROQUINONE 4 g/100 g

141060 HYDROCORTISONE 0.5% / HYDROQUINONE 4% / TRETINOIN 0.025%